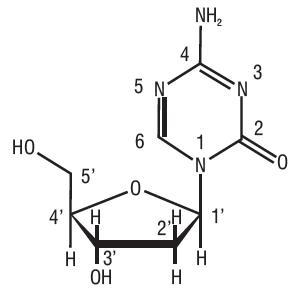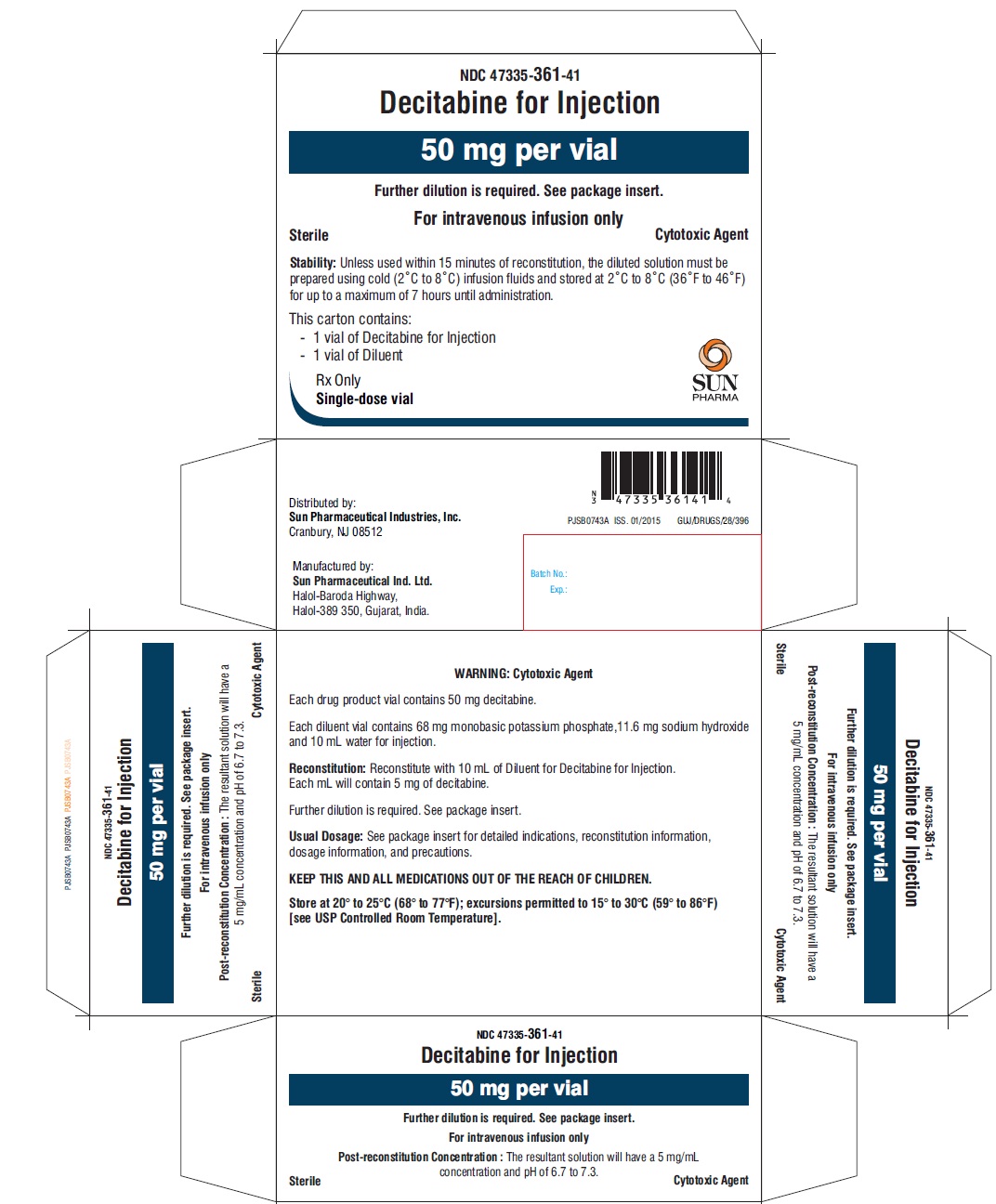 DRUG LABEL: decitabine
NDC: 47335-361 | Form: KIT | Route: INTRAVENOUS
Manufacturer: Sun Pharmaceutical Industries, Inc.
Category: prescription | Type: Human Prescription Drug Label
Date: 20200723

ACTIVE INGREDIENTS: DECITABINE 50 mg/10 mL
INACTIVE INGREDIENTS: MONOBASIC POTASSIUM PHOSPHATE; SODIUM HYDROXIDE; WATER

HIGHLIGHTS OF PRESCRIBING INFORMATION

These highlights do not include all the information needed to use DECITABINE FOR INJECTION safely and effectively. See full prescribing information for DECITABINE FOR INJECTION.
DECITABINE for injection, for intravenous use
Initial U.S. Approval: 2006

1 INDICATIONS AND USAGE

Decitabine for Injection is a nucleoside metabolic inhibitor indicated for treatment of adult patients with myelodysplastic syndromes (MDS) including previously treated and untreated, de novo and secondary MDS of all French-American-British subtypes (refractory anemia, refractory anemia with ringed sideroblasts, refractory anemia with excess blasts, refractory anemia with excess blasts in transformation, and chronic myelomonocytic leukemia) and intermediate-1, intermediate-2, and high-risk International Prognostic Scoring System groups. (1)

2 DOSAGE AND ADMINISTRATION

- Three Day Regimen: Administer Decitabine for Injection at a dose of 15 mg/m^2 by continuous intravenous infusion over 3 hours repeated every 8 hours for 3 days. Repeat cycle every 6 weeks. (2.1)

- Five Day Regimen: Administer Decitabine for Injection at a dose of 20 mg/m^2 by continuous intravenous infusion over 1 hour repeated daily for 5 days. Repeat cycle every 4 weeks.(2.1)

3 DOSAGE FORMS AND STRENGTHS

For Injection: 50 mg of decitabine as a lyophilized powder in a single-dose vial for reconstitution with the supplied diluent. (3)

4 CONTRAINDICATIONS

None

5 WARNINGS AND PRECAUTIONS

- Neutropenia and Thrombocytopenia: Perform complete blood counts and platelet counts. (5.1)
- Embryo-Fetal Toxicity: Can cause fetal harm. Advise patients of reproductive potential of the potential risk to a fetus and to use effective contraception (5.2, 8.1, 8.3)

6 ADVERSE REACTIONS

Most common adverse reactions (> 50%) are neutropenia, thrombocytopenia, anemia, and pyrexia. (6.1)

To report SUSPECTED ADVERSE REACTIONS, contact Sun Pharmaceutical Industries, Inc. at 1-800-818-4555 or FDA at 1-800-FDA-1088 or www.fda.gov/medwatch.

8 USE IN SPECIFIC POPULATIONS

Lactation: Advise not to breastfeed. (8.2)

FULL PRESCRIBING INFORMATION

1 INDICATIONS AND USAGE

Decitabine for Injection is indicated for treatment of adult patients with myelodysplastic syndromes (MDS) including previously treated and untreated, de novo and secondary MDS of all French-American-British subtypes (refractory anemia, refractory anemia with ringed sideroblasts, refractory anemia with excess blasts, refractory anemia with excess blasts in transformation, and chronic myelomonocytic leukemia) and intermediate-1, intermediate-2, and high-risk International Prognostic Scoring System groups.

2 DOSAGE AND ADMINISTRATION

2.1 Recommended Dosage

Pre-Medications and Baseline Testing

- Consider pre-medicating for nausea with antiemetics.
- Conduct baseline laboratory testing: complete blood count (CBC) with platelets, serum hepatic panel, and serum creatinine.

Decitabine for Injection Regimen Options

Three Day Regimen

Administer Decitabine for Injection at a dose of 15 mg/m^2 by continuous intravenous infusion over 3 hours repeated every 8 hours for 3 days. Repeat cycles every 6 weeks upon hematologic recovery (ANC at least 1,000/μL and platelets at least 50,000/μL) for a minimum of 4 cycles. A complete or partial response may take longer than 4 cycles. Delay and reduce dose for hematologic toxicity [see Dosage and Administration (2.2)].

Five Day Regimen

Administer Decitabine for Injection at a dose of 20 mg/m^2 by continuous intravenous infusion over 1 hour daily for 5 days. Delay and reduce dose for hematologic toxicity [see Dosage and Administration (2.2)]. Repeat cycles every 4 weeks upon hematologic recovery (ANC at least 1,000/μL and platelets at least 50,000/μL) for a minimum of 4 cycles. A complete or partial response may take longer than 4 cycles.

Patients with Renal or Severe Hepatic Impairment

Treatment with decitabine has not been studied in patients with pre-existing renal or hepatic impairment. For patients with pre-existing renal or hepatic impairment, consider the potential risks and benefits before initiating treatment with Decitabine for Injection.

2.2 Dosage Modifications for Adverse Reactions

Hematologic Toxicity

If hematologic recovery from a previous treatment cycle requires more than 6 weeks, delay the next cycle and reduce the dose temporarily by following this algorithm:

- Recovery requiring more than 6, but less than 8 weeks: delay dosing for up to 2 weeks and reduce the dose of Decitabine for Injection temporarily to 11 mg/m^2 every 8 hours (33 mg/m^2/day, 99 mg/m^2/cycle) upon restarting therapy.
- Recovery requiring more than 8, but less than 10 weeks: Perform bone marrow aspirate to assess for disease progression. In the absence of progression, delay dosing up to 2 more weeks and reduce the dose to 11 mg/m^2 every 8 hours (33 mg/m^2/day, 99 mg/m^2/cycle) upon restarting therapy, then maintain or increase dose in subsequent cycles as clinically indicated.

Non-hematologic Toxicity

Delay subsequent treatment for any the following non-hematologic toxicities and do not restart until toxicities resolve:

- Serum creatinine greater than or equal to 2 mg/dL
- Alanine transaminase (ALT), total bilirubin greater than or equal to 2 times upper limit of normal (ULN)
- Active or uncontrolled infection

2.3 Preparation and Administration

Decitabine for Injection is a cytotoxic drug. Follow special handling and disposal procedures.^1

Aseptically reconstitute Decitabine for Injection with room temperature (20°C to 25°C) 10 mL of diluent for Decitabine for Injection. Upon reconstitution, the final concentration of the reconstituted decitabine solution is 5 mg/mL. Dilute the reconstituted solution with 0.9% Sodium Chloride Injection or 5% Dextrose Injection prior to administration. Temperature of the diluent (0.9% Sodium Chloride Injection or 5% Dextrose Injection) depends on time of administration after preparation.

For Administration Within 15 Minutes of Preparation

If Decitabine for Injection is intended to be administered within 15 minutes from the time of preparation, dilute the reconstituted solution with room temperature (20°C to 25°C) 0.9% Sodium Chloride Injection or 5% Dextrose Injection to a final concentration of 0.1 mg/mL to 1 mg/mL. Discard unused portion.

For Delayed Administration

If Decitabine for Injection is intended to be administered after 15 minutes of preparation, dilute the reconstituted solution with cold (2°C to 8°C) 0.9% Sodium Chloride Injection or 5% Dextrose Injection to a final concentration of 0.1 mg/mL to 1 mg/mL. Store at 2°C to 8°C for up to 7 hours. Diluted stored solution must be used within 7 hours from the time of preparation. Use the diluted, refrigerated solution within 7 hours from the time of preparation or discard. Discard unused portion.

Parenteral drug products should be inspected visually for particulate matter and discoloration prior to administration, whenever solution and container permit. Do not use if there is evidence of particulate matter or discoloration.

3 DOSAGE FORMS AND STRENGTHS

For Injection: 50 mg of decitabine as a sterile, lyophilized white to off white powder in a single-dose vial for reconstitution with the supplied diluent.

4 CONTRAINDICATIONS

None

5 WARNINGS AND PRECAUTIONS

5.1 Myelosuppression

Fatal and serious myelosuppression occurs in Decitabine for Injection-treated patients. Myelosuppression (anemia, neutropenia, and thrombocytopenia) is the most frequent cause of dose reduction, delay, and discontinuation. Neutropenia of any grade occurred in 90% of decitabine-treated patients with grade 3 or 4 occurring in 87% of patients. Grade 3 or 4 febrile neutropenia occurred in 23% of patients. Thrombocytopenia of any grade occurred in 89% of patients with grade 3 or 4 occurring in 85% of patients. Anemia of any grade occurred in 82% of patients.

Perform complete blood count with platelets at baseline, prior to each cycle, and as needed to monitor response and toxicity. Manage toxicity using dose-delay, dose-reduction, growth factors, and anti-infective therapies as needed [see Dosage and Administration (2.2)]. Myelosuppression and worsening neutropenia may occur more frequently in the first or second treatment cycles and may not necessarily indicate progression of underlying MDS.

5.2 Embryo-Fetal Toxicity

Based on findings from human data, animal studies and its mechanism of action, Decitabine for Injection can cause fetal harm when administered to a pregnant woman [see Clinical Pharmacology (12.1) and Nonclinical Toxicology (13.1)]. In preclinical studies in mice and rats, decitabine caused adverse developmental outcomes including embryo-fetal lethality and malformations. Advise pregnant women of the potential risk to a fetus. Advise females of reproductive potential to use effective contraception while receiving Decitabine for Injection and for 6 months following the last dose. Advise males with female partners of reproductive potential to use effective contraception while receiving treatment with Decitabine for Injection and for 3 months following the last dose [see Use in Specific Populations (8.1, 8.3)].

6 ADVERSE REACTIONS

The following clinically significant adverse reactions are described elsewhere in the labeling:

- Myelosuppression [see Warnings and Precautions (5.1)]

6.1 Clinical Trials Experience

Because clinical trials are conducted under widely varying conditions, adverse reaction rates observed in the clinical trials of a drug cannot be directly compared to rates in the clinical trials of another drug and may not reflect the rates observed in practice.

The safety of decitabine was studied in 3 single-arm studies (N = 66, N = 98, N = 99) and 1 controlled supportive care study (N = 83 decitabine, N = 81 supportive care). The data described below reflect exposure to decitabine in 83 patients in the MDS trial. In the trial, patients received 15 mg/m^2 intravenously every 8 hours for 3 days every 6 weeks. The median number of cycles was 3 (range 0 to 9).
Most Common Adverse Reactions: neutropenia, thrombocytopenia, anemia, fatigue, pyrexia, nausea, cough, petechiae, constipation, diarrhea, and hyperglycemia.

Adverse Reactions Most Frequently (≥ 1%) Resulting in Clinical Intervention and or Dose Modification in the Controlled Supportive Care Study in the Decitabine Arm:

- Discontinuation: thrombocytopenia, neutropenia, pneumonia, Mycobacterium avium complex infection, cardio-respiratory arrest, increased blood bilirubin, intracranial hemorrhage, abnormal liver function tests.
- Dose Delayed: neutropenia, pulmonary edema, atrial fibrillation, central line infection, febrile neutropenia.
- Dose Reduced: neutropenia, thrombocytopenia, anemia, lethargy, edema, tachycardia, depression, pharyngitis.

Table 1 presents all adverse reactions occurring in at least 5% of patients in the decitabine group and at a rate greater than supportive care.

Table 1 Adverse Reactions Reported in ≥ 5% of Patients in the Decitabine Group and at a Rate Greater than Supportive Care in the Controlled Trial in MDS

 | Decitabine N = 83 (%) | Supportive Care N = 81 (%)
Blood and lymphatic system disorders
Neutropenia | 75 (90) | 58 (72)
Thrombocytopenia | 74 (89) | 64 (79)
Anemia NOS | 68 (82) | 60 (74)
Febrile neutropenia | 24 (29) | 5 (6)
Leukopenia NOS | 23 (28) | 11 (14)
Lymphadenopathy | 10 (12) | 6 (7)
Thrombocythemia | 4 (5) | 1 (1)
Cardiac disorders
Pulmonary edema NOS | 5 (6) | 0 (0)
Eye disorders
Vision blurred | 5 (6) | 0 (0)
Gastrointestinal disorders
Nausea | 35 (42) | 13 (16)
Constipation | 29 (35) | 11 (14)
Diarrhea NOS | 28 (34) | 13 (16)
Vomiting NOS | 21 (25) | 7 (9)
Abdominal pain NOS | 12 (14) | 5 (6)
Oral mucosal petechiae | 11 (13) | 4 (5)
Stomatitis | 10 (12) | 5 (6)
Dyspepsia | 10 (12) | 1 (1)
Ascites | 8 (10) | 2 (2)
Gingival bleeding | 7 (8) | 5 (6)
Hemorrhoids | 7 (8) | 3 (4)
Loose stools | 6 (7) | 3 (4)
Tongue ulceration | 6 (7) | 2 (2)
Dysphagia | 5 (6) | 2 (2)
Oral soft tissue disorder NOS | 5 (6) | 1 (1)
Lip ulceration | 4 (5) | 3 (4)
Abdominal distension | 4 (5) | 1 (1)
Abdominal pain upper | 4 (5) | 1 (1)
Gastro-esophageal reflux disease | 4 (5) | 0 (0)
Glossodynia | 4 (5) | 0 (0)
General disorders and administrative site disorders
Pyrexia | 44 (53) | 23 (28)
Edema peripheral | 21 (25) | 13 (16)
Rigors | 18 (22) | 14 (17)
Edema NOS | 15 (18) | 5 (6)
Pain NOS | 11 (13) | 5 (6)
Lethargy | 10 (12) | 3 (4)
Tenderness NOS | 9 (11) | 0 (0)
Fall | 7 (8) | 3 (4)
Chest discomfort | 6 (7) | 3 (4)
Intermittent pyrexia | 5 (6) | 3 (4)
Malaise | 4 (5) | 1 (1)
Crepitations NOS | 4 (5) | 1 (1)
Catheter site erythema | 4 (5) | 1 (1)
Catheter site pain | 4 (5) | 0 (0)
Injection site swelling | 4 (5) | 0 (0)
Hepatobiliary disorders
Hyperbilirubinemia | 12 (14) | 4 (5)
Infections and infestations
Pneumonia NOS | 18 (22) | 11 (14)
Cellulitis | 10 (12) | 6 (7)
Candidal infection NOS | 8 (10) | 1 (1)
Catheter related infection | 7 (8) | 0 (0)
Urinary tract infection NOS | 6 (7) | 1 (1)
Staphylococcal infection | 6 (7) | 0 (0)
Oral candidiasis | 5 (6) | 2 (2)
Sinusitis NOS | 4 (5) | 2 (2)
Bacteremia | 4 (5) | 0 (0)
Injury, poisoning and procedural complications
Transfusion reaction | 6 (7) | 3 (4)
Abrasion NOS | 4 (5) | 1 (1)
Investigations
Cardiac murmur NOS | 13 (16) | 9 (11)
Blood alkaline phosphatase NOS increased | 9 (11) | 7 (9)
Aspartate aminotransferase increased | 8 (10) | 7 (9)
Blood urea increased | 8 (10) | 1 (1)
Blood lactate dehydrogenase increased | 7 (8) | 5 (6)
Blood albumin decreased | 6 (7) | 0 (0)
Blood bicarbonate increased | 5 (6) | 1 (1)
Blood chloride decreased | 5 (6) | 1 (1)
Protein total decreased | 4 (5) | 3 (4)
Blood bicarbonate decreased | 4 (5) | 1 (1)
Blood bilirubin decreased | 4 (5) | 1 (1)
Metabolism and nutrition disorders
Hyperglycemia NOS | 27 (33) | 16 (20)
Hypoalbuminemia | 20 (24) | 14 (17)
Hypomagnesemia | 20 (24) | 6 (7)
Hypokalemia | 18 (22) | 10 (12)
Hyponatremia | 16 (19) | 13 (16)
Appetite decreased NOS | 13 (16) | 12 (15)
Anorexia | 13 (16) | 8 (10)
Hyperkalemia | 11 (13) | 3 (4)
Dehydration | 5 (6) | 4 (5)
Musculoskeletal and connective tissue disorders
Arthralgia | 17 (20) | 8 (10)
Pain in limb | 16 (19) | 8 (10)
Back pain | 14 (17) | 5 (6)
Chest wall pain | 6 (7) | 1 (1)
Musculoskeletal discomfort | 5 (6) | 0 (0)
Myalgia | 4 (5) | 1 (1)
Nervous system disorders
Headache | 23 (28) | 11 (14)
Dizziness | 15 (18) | 10 (12)
Hypoesthesia | 9 (11) | 1 (1)
Psychiatric disorders
Insomnia | 23 (28) | 11 (14)
Confusional state | 10 (12) | 3 (4)
Anxiety | 9 (11) | 8 (10)
Renal and urinary disorders
Dysuria | 5 (6) | 3 (4)
Urinary frequency | 4 (5) | 1 (1)
Respiratory, thoracic and Mediastinal disorders
Cough | 33 (40) | 25 (31)
Pharyngitis | 13 (16) | 6 (7)
Crackles lung | 12 (14) | 1 (1)
Breath sounds decreased | 8 (10) | 7 (9)
Hypoxia | 8 (10) | 4 (5)
Rales | 7 (8) | 2 (2)
Postnasal drip | 4 (5) | 2 (2)
Skin and subcutaneous tissue disorders
Ecchymosis | 18 (22) | 12 (15)
Rash NOS | 16 (19) | 7 (9)
Erythema | 12 (14) | 5 (6)
Skin lesion NOS | 9 (11) | 3 (4)
Pruritis | 9 (11) | 2 (2)
Alopecia | 7 (8) | 1 (1)
Urticaria NOS | 5 (6) | 1 (1)
Swelling face | 5 (6) | 0 (0)
Vascular disorders
Petechiae | 32 (39) | 13 (16)
Pallor | 19 (23) | 10 (12)
Hypotension NOS | 5 (6) | 4 (5)
Hematoma NOS | 4 (5) | 3 (4)

In a single-arm MDS study (N=99) decitabine was dosed at 20 mg/m^2 intravenously, infused over one hour daily, for 5 consecutive days of a 4-week cycle. Table 2 presents all adverse reactions occurring in at least 5% of patients.

Table 2 Adverse Reactions Reported in ≥ 5% of Patients in a Single-arm Study^1

 | Decitabine N = 99 (%)
Blood and lymphatic system disorders
Anemia | 31 (31)
Febrile neutropenia | 20 (20)
Leukopenia | 6 (6)
Neutropenia | 38 (38)
Pancytopenia | 5 (5)
Thrombocythemia | 5 (5)
Thrombocytopenia | 27 (27)
Cardiac disorders
Cardiac failure congestive | 5 (5)
Tachycardia | 8 (8)
Ear and labyrinth disorders
Ear pain | 6 (6)
Gastrointestinal disorders
Abdominal pain | 14 (14)
Abdominal pain upper | 6 (6)
Constipation | 30 (30)
Diarrhea | 28 (28)
Dyspepsia | 10 (10)
Dysphagia | 5 (5)
Gastro-esophageal reflux disease | 5 (5)
Nausea | 40 (40)
Oral pain | 5 (5)
Stomatitis | 11 (11)
Toothache | 6 (6)
Vomiting | 16 (16)
General disorders and administration site conditions
Asthenia | 15 (15)
Chest pain | 6 (6)
Chills | 16 (16)
Fatigue | 46 (46)
Mucosal inflammation | 9 (9)
Edema | 5 (5)
Edema peripheral | 27 (27)
Pain | 5 (5)
Pyrexia | 36 (36)
Infections and infestations
Cellulitis | 9 (9)
Oral candidiasis | 6 (6)
Pneumonia | 20 (20)
Sinusitis | 6 (6)
Staphylococcal bacteremia | 8 (8)
Tooth abscess | 5 (5)
Upper respiratory tract infection | 10 (10)
Urinary tract infection | 7 (7)
Injury, poisoning and procedural complications
Contusion | 9 (9)
Investigations
Blood bilirubin increased | 6 (6)
Breath sounds abnormal | 5 (5)
Weight decreased | 9 (9)
Metabolism and nutrition disorders
Anorexia | 23 (23)
Decreased appetite | 8 (8)
Dehydration | 8 (8)
Hyperglycemia | 6 (6)
Hypokalemia | 12 (12)
Hypomagnesemia | 5 (5)
Musculoskeletal and connective tissue disorders
Arthralgia | 17 (17)
Back pain | 18 (18)
Bone pain | 6 (6)
Muscle spasms | 7 (7)
Muscular weakness | 5 (5)
Musculoskeletal pain | 5 (5)
Myalgia | 9 (9)
Pain in extremity | 18 (18)
Nervous system disorders
Dizziness | 21 (21)
Headache | 23 (23)
Psychiatric disorders
Anxiety | 9 (9)
Confusional state | 8 (8)
Depression | 9 (9)
Insomnia | 14 (14)
Respiratory, thoracic and mediastinal disorders
Cough | 27 (27)
Dyspnea | 29 (29)
Epistaxis | 13 (13)
Pharyngolaryngeal pain | 8 (8)
Pleural effusion | 5 (5)
Sinus congestion | 5 (5)
Skin and subcutaneous tissue disorders
Dry skin | 8 (8)
Ecchymosis | 9 (9)
Erythema | 5 (5)
Night sweats | 5 (5)
Petechiae | 12 (12)
Pruritus | 9 (9)
Rash | 11 (11)
Skin lesion | 5 (5)
Vascular disorders
Hypertension | 6 (6)
Hypotension | 11 (11)

^1In this single arm study, investigators reported adverse events based on clinical signs and symptoms rather than predefined laboratory abnormalities. Thus, not all laboratory abnormalities were recorded as adverse events.

No overall difference in safety was detected between patients > 65 years of age and younger patients in these MDS trials. No significant differences in safety were detected between males and females. Patients with renal or hepatic dysfunction were not studied. Insufficient numbers of non-White patients were available to draw conclusions in these clinical trials.

Serious adverse reactions that occurred in patients receiving decitabine not previously reported in Tables 1 and 2 include:

- Allergic Reaction: hypersensitivity (anaphylactic reaction)
- Blood and Lymphatic System Disorders: myelosuppression, splenomegaly
- Cardiac Disorders: myocardial infarction, cardio-respiratory arrest, cardiomyopathy, atrial fibrillation, supraventricular tachycardia
- Gastrointestinal Disorders: gingival pain, upper gastrointestinal hemorrhage
- General Disorders and Administrative Site Conditions: chest pain, catheter site hemorrhage
- Hepatobiliary Disorders: cholecystitis
- Infections and Infestations: fungal infection, sepsis, bronchopulmonary aspergillosis, peridiverticular abscess, respiratory tract infection, pseudomonal lung infection, Mycobacterium avium complex infection
- Injury, Poisoning and Procedural Complications: post procedural pain, post procedural hemorrhage
- Nervous System Disorders: intracranial hemorrhage
- Psychiatric Disorders: mental status changes
- Renal and Urinary Disorders: renal failure, urethral hemorrhage
- Respiratory, Thoracic and Mediastinal Disorders: hemoptysis, lung infiltration, pulmonary embolism, respiratory arrest, pulmonary mass

6.2 Postmarketing Experience

The following adverse reactions have been identified during postapproval use of decitabine. Because these reactions are reported voluntarily from a population of uncertain size, it is not always possible to reliably estimate their frequency or establish a causal relationship to drug exposure.

- Sweet’s syndrome (acute febrile neutrophilic dermatosis)
- Differentiation syndrome
- Interstitial lung disease

7 DRUG INTERACTIONS

Drug interaction studies with decitabine have not been conducted. In vitro studies in human liver microsomes suggest that decitabine is unlikely to inhibit or induce cytochrome P450 enzymes. In vitro metabolism studies have suggested that decitabine is not a substrate for human liver cytochrome P450 enzymes. As plasma protein binding of decitabine is negligible (<1%), interactions due to displacement of more highly protein bound drugs from plasma proteins are not expected.

8 USE IN SPECIFIC POPULATIONS

8.1 Pregnancy

Risk Summary

Based on findings from human data, animal studies, and the mechanism of action, Decitabine for Injection can cause fetal harm when administered to a pregnant woman [see Clinical Pharmacology (12.1) and Nonclinical Toxicology (13.1)]. Limited published data on decitabine use throughout the first trimester during pregnancy describe adverse developmental outcomes including major birth defects (structural abnormalities). In animal reproduction studies, administration of decitabine to pregnant mice and rats during organogenesis caused adverse developmental outcomes including malformations and embryo-fetal lethality starting at doses approximately 7% of the recommended human dose on a mg/m^2 basis (see Data). Advise pregnant women of the potential risk to a fetus.

The estimated background risk of major birth defects and miscarriage for the indicated population is unknown. All pregnancies have a background risk of birth defect, loss, or other adverse outcomes. The estimated background risk of major birth defects and miscarriage in the U.S. general population is 2% to 4% and 15% to 20% of clinically recognized pregnancies, respectively.

Data

Human Data

A single published case report of decitabine pregnancy exposure in a 39-year old woman with a hematologic malignancy described multiple structural abnormalities after 6 cycles of therapy in the 18th week of gestation. These abnormalities included holoprosencephaly, absence of nasal bone, mid-facial deformity, cleft lip and palate, polydactyly and rocker-bottom feet. The pregnancy was terminated.

Animal Data

In utero exposure to decitabine causes temporal related defects in the rat and/or mouse, which include growth suppression, exencephaly, defective skull bones, rib/sternabrae defects, phocomelia, digit defects, micrognathia, gastroschisis, micromelia. Decitabine inhibits proliferation and increases apoptosis of neural progenitor cells of the fetal CNS and induces palatal clefting in the developing murine fetus. Studies in mice have also shown that decitabine administration during osteoblastogenesis (day 10 of gestation) induces bone loss in offspring.

In mice exposed to single IP (intraperitoneal) injections (0, 0.9 and 3.0 mg/m^2, approximately 2% and 7% of the recommended daily clinical dose, respectively) over gestation days 8, 9, 10 or 11, no maternal toxicity was observed but reduced fetal survival was observed after treatment at 3 mg/m^2 and decreased fetal weight was observed at both dose levels. The 3 mg/m^2 dose elicited characteristic fetal defects for each treatment day, including supernumerary ribs (both dose levels), fused vertebrae and ribs, cleft palate, vertebral defects, hind-limb defects and digital defects of fore- and hind-limbs.

In rats given a single IP injection of 2.4, 3.6 or 6 mg/m^2 (approximately 5%, 8%, or 13% the daily recommended clinical dose, respectively) on gestation days 9 to 12, no maternal toxicity was observed. No live fetuses were seen at any dose when decitabine was injected on gestation day 9. A significant decrease in fetal survival and reduced fetal weight at doses greater than 3.6 mg/m^2 was seen when decitabine was given on gestation day 10. Increased incidences of vertebral and rib anomalies were seen at all dose levels, and induction of exophthalmia, exencephaly, and cleft palate were observed at 6.0 mg/m^2. Increased incidence of foredigit defects was seen in fetuses at doses greater than 3.6 mg/m^2. Reduced size and ossification of long bones of the fore-limb and hind-limb were noted at 6.0 mg/m^2.

The effect of decitabine on postnatal development and reproductive capacity was evaluated in mice administered a single 3 mg/m^2 IP injection (approximately 7% the recommended daily clinical dose) on day 10 of gestation. Body weights of males and females exposed in utero to decitabine were significantly reduced relative to controls at all postnatal time points. No consistent effect on fertility was seen when female mice exposed in utero were mated to untreated males. Untreated females mated to males exposed in utero showed decreased fertility at 3 and 5 months of age (36% and 0% pregnancy rate, respectively). Follow up studies indicated that treatment of pregnant mice with decitabine on gestation day 10 was associated with a reduced pregnancy rate resulting from effects on sperm production in the F1-generation.

8.2 Lactation

Risk Summary

There are no data on the presence of decitabine or its metabolites in human milk, the effects on the breastfed child, or the effects on milk production. Because of the potential for serious adverse reactions from decitabine in a breastfed child, advise women not to breastfeed while receiving Decitabine for Injection and for at least 2 weeks after the last dose.

8.3 Females and Males of Reproductive Potential

Pregnancy Testing

Conduct pregnancy testing of females of reproductive potential prior to initiating Decitabine for njection.

ContraceptionI

Females

Decitabine for Injection can cause fetal harm when administered to pregnant women [see Use in Specific Populations (8.1)]. Advise females of reproductive potential to use effective contraception while receiving Decitabine for Injection and for 6 months following the last dose.

Males

Advise males with female partners of reproductive potential to use effective contraception while receiving treatment with Decitabine for Injection and for 3 months following the last dose [see Nonclinical Toxicology (13.1)].

Infertility

Based on findings of decitabine in animals, male fertility may be compromised by treatment with decitabine. The reversibility of the effect on fertility is unknown [see Nonclinical Toxicology (13.1)].

8.4 Pediatric Use

The safety and effectiveness of Decitabine for Injection in pediatric patients have not been established.

8.5 Geriatric Use

Of the total number of patients exposed to decitabine in the controlled clinical trial, 61 of 83 patients were age 65 years and over, while 21 of 83 patients were age 75 years and over. No overall differences in safety or effectiveness were observed between these subjects and younger subjects, and other reported clinical experience has not identified differences in responses between the elderly and younger patients, but greater sensitivity of some older individuals cannot be ruled out.

10 OVERDOSAGE

There is no known antidote for overdosage with decitabine. Higher doses are associated with increased myelosuppression including prolonged neutropenia and thrombocytopenia. Standard supportive measures should be taken in the event of an overdose.

11 DESCRIPTION

Decitabine is a nucleoside metabolic inhibitor. Decitabine is a fine, white to almost white powder with the molecular formula of C8H12N4O4 and a molecular weight of 228.21. Its chemical name is 4-amino-1-(2-deoxy-β-D-erythro-pentofuranosyl)-1,3,5-triazin-2(1H)-one and it has the following structural formula:

Decitabine is slightly soluble in ethanol/water (50/50), methanol/water (50/50) and methanol; sparingly soluble in water and soluble in dimethylsulfoxide (DMSO).

DRUG PRODUCT

White to off white lyophilized powder in 20 mL colorless tubular glass single-dose vial with grey bromo butyl rubber stopper and sealed with baby blue flip top aluminum seal.

Each vial contains 50 mg decitabine.

DILUENT

Clear colorless solution filled in 10 mL colorless tubular glass vial with grey bromo butyl stopper sealed with transparent flip top aluminum seal.

Each vial contains 68 mg monobasic potassium phosphate, 11.6 mg sodium hydroxide and 10 mL water for injection.

12 CLINICAL PHARMACOLOGY

12.1 Mechanism of Action

Decitabine is believed to exert its antineoplastic effects after phosphorylation and direct incorporation into DNA and inhibition of DNA methyltransferase, causing hypomethylation of DNA and cellular differentiation or apoptosis. Decitabine inhibits DNA methylation in vitro, which is achieved at concentrations that do not cause major suppression of DNA synthesis. Decitabine-induced hypomethylation in neoplastic cells may restore normal function to genes that are critical for the control of cellular differentiation and proliferation. In rapidly dividing cells, the cytotoxicity of decitabine may also be attributed to the formation of covalent adducts between DNA methyltransferase and decitabine incorporated into DNA. Non-proliferating cells are relatively insensitive to decitabine.

12.2 Pharmacodynamics

Decitabine has been shown to induce hypomethylation both in vitro and in vivo. However, there have been no studies of decitabine-induced hypomethylation and pharmacokinetic parameters.

12.3 Pharmacokinetics

Pharmacokinetic (PK) parameters were evaluated in patients. Eleven patients received 20 mg/m^2 infused over 1 hour intravenously (treatment Option 2). Fourteen patients received 15 mg/m^2 infused over 3 hours intravenously (treatment Option 1). PK parameters are shown in Table 3. Plasma concentration-time profiles after discontinuation of infusion showed a biexponential decline. The clearance (CL) of decitabine was higher following treatment Option 2. Upon repeat doses, there was no systemic accumulation of decitabine or any changes in PK parameters. Population PK analysis (N=35) showed that the cumulative AUC per cycle for treatment Option 2 was 2.3-fold lower than the cumulative AUC per cycle following treatment Option 1.

Table 3 Mean (CV% or 95% CI) Pharmacokinetic Parameters of Decitabine

Dose | Cmax (ng/mL) | AUC0-INF (ng·h/mL) | T½ (h) | CL (L/h/m^2) | AUCCumulative (ng·h/mL) [N=35 Cumulative AUC per cycle]
15 mg/m^2 3-hr infusion every 8 hours for 3 days (Option 1) [N=14] | 73.8 (66) | 163 (62) | 0.62 (49) | 125 (53) | 1332 (1010 to 1730)
20 mg/m^2 1-hr infusion daily for 5 days (Option 2) [N=11] | 147 (49) | 115 (43) | 0.54 (43) | 210 (47) | 570 (470 to 700)

The exact route of elimination and metabolic fate of decitabine is not known in humans. One of the pathways of elimination of decitabine appears to be deamination by cytidine deaminase found principally in the liver but also in granulocytes, intestinal epithelium and whole blood.

Specific Populations

Patients with Renal Impairment

There are no data on the use of decitabine in patients with renal impairment.

Patients with Hepatic Impairment

There are no data on the use of decitabine in patients with hepatic impairment.

13 NONCLINICAL TOXICOLOGY

13.1 Carcinogenesis, Mutagenesis and Impairment of Fertility

Carcinogenicity studies with decitabine have not been conducted.

The mutagenic potential of decitabine was tested in several in vitro and in vivo systems. Decitabine increased mutation frequency in L5178Y mouse lymphoma cells, and mutations were produced in an Escherichia coli lac-I transgene in colonic DNA of decitabine-treated mice. Decitabine caused chromosomal rearrangements in larvae of fruit flies.

In male mice given IP injections of 0.15, 0.3 or 0.45 mg/m^2 decitabine (approximately 0.3% to 1% the recommended clinical dose) 3 times a week for 7 weeks, decitabine did not affect survival, body weight gain or hematological measures (hemoglobin and white blood cell counts). Testes weights were reduced, abnormal histology was observed and significant decreases in sperm number were found at doses ≥ 0.3 mg/m^2. In females mated to males dosed with ≥ 0.3 mg/m^2 decitabine, pregnancy rate was reduced and preimplantation loss was significantly increased.

14 CLINICAL STUDIES

14.1 Controlled Trial in Myelodysplastic Syndrome

A randomized open-label, multicenter, controlled trial evaluated 170 adult patients with myelodysplastic syndromes (MDS) meeting French-American-British (FAB) classification criteria and International Prognostic Scoring System (IPSS) High-Risk, Intermediate-2 and Intermediate-1 prognostic scores. Eighty-nine patients were randomized to decitabine plus supportive care (only 83 received decitabine), and 81 to Supportive Care (SC) alone. Patients with Acute Myeloid Leukemia (AML) were not intended to be included. Of the 170 patients included in the study, independent review (adjudicated diagnosis) found that 12 patients (9 in the decitabine group and 3 in the SC group) had the diagnosis of AML at baseline. Baseline demographics and other patient characteristics in the Intent-to-Treat (ITT) population were similar between the 2 groups, as shown in Table 4.

Table 4 Baseline Demographics and Other Patient Characteristics (ITT)

Demographic or Other Patient Characteristic | Decitabine N = 89 | Supportive Care N= 81
Age (years)
Mean (±SD) | 69±10 | 67±10
Median (IQR) | 70 (65 to 76) | 70 (62 to 74)
(Range: min-max) | (31 to 85) | (30 to 82)
Sex n (%)
Male | 59 (66) | 57 (70)
Female | 30 (34) | 24 (30)
Race n (%)
White | 83 (93) | 76 (94)
Black | 4 (4) | 2 (2)
Other | 2 (2) | 3 (4)
Weeks Since MDS Diagnosis
Mean (±SD) | 86±131 | 77±119
Median (IQR) | 29 (10 to 87) | 35 (7 to 98)
(Range: min-max) | (2 to 667) | (2 to 865)
Previous MDS Therapy n (%)
Yes | 27 (30) | 19 (23)
No | 62 (70) | 62 (77)
RBC Transfusion Status n (%)
Independent | 23 (26) | 27 (33)
Dependent | 66 (74) | 54 (67)
Platelet Transfusion Status n (%)
Independent | 69 (78) | 62 (77)
Dependent | 20 (22) | 19 (23)
IPSS Classification n (%)
Intermediate–1 | 28 (31) | 24 (30)
Intermediate–2 | 38 (43) | 36 (44)
High Risk | 23 (26) | 21 (26)
FAB Classification n (%)
RA | 12 (13) | 12 (15)
RARS | 7 (8) | 4 (5)
RAEB | 47 (53) | 43 (53)
RAEB-t | 17 (19) | 14 (17)
CMML | 6 (7) | 8 (10)

Patients randomized to the decitabine group received decitabine intravenously infused at a dose of 15 mg/m^2 over a 3-hour period, every 8 hours, for 3 consecutive days. This cycle was repeated every 6 weeks, depending on the patient’s clinical response and toxicity. Supportive care consisted of blood and blood product transfusions, prophylactic antibiotics, and hematopoietic growth factors. The study endpoints were overall response rate (complete response + partial response) and time to AML or death. Responses were classified using the MDS International Working Group (IWG) criteria; patients were required to be RBC and platelet transfusion independent during the time of response. Response criteria are given in Table 5.

Table 5 Response Criteria for the Controlled Trial in MDS*

Complete Response (CR) ≥ 8 weeks | Bone Marrow | On repeat aspirates:; - < 5% myeloblasts - No dysplastic changes
Complete Response (CR) ≥ 8 weeks | Peripheral Blood | In all samples during response:; - Hgb > 11 g/dL (no transfusions or erythropoietin - ANC ≥ 1500/µL (no growth factor) - Platelets ≥ 100,000/ µL (no thrombopoietic agent) - No blasts and no dysplasia
Partial Response (PR) ≥ 8 weeks | Bone Marrow | On repeat aspirates:; - ≥ 50% decrease in blasts over pretreatment values; OR; - Improvement to a less advanced MDS FAB classification
Partial Response (PR) ≥ 8 weeks | Peripheral Blood | Same as for CR

*Cheson BD, Bennett JM, et al. Report of an International Working Group to Standardize Response Criteria for MDS. Blood. 2000; 96:3671-3674.

The overall response rate (CR+PR) in the ITT population was 17% in decitabine group and 0% in the SC group (p<0.001) (see Table 6). The overall response rate was 21% (12/56) in decitabine-treated patients considered evaluable for response (i.e., those patients with pathologically confirmed MDS at baseline who received at least 2 cycles of treatment). The median duration of response (range) for patients who responded to decitabine was 288 days (116 to 388) and median time to response (range) was 93 days (55 to 272). All but one of the decitabine-treated patients who responded did so by the fourth cycle. Benefit was seen in an additional 13% of decitabine-treated patients who had hematologic improvement, defined as a response less than PR lasting at least 8 weeks, compared to 7% of SC patients. Treatment did not significantly delay the median time to AML or death versus supportive care.

Table 6 Analysis of Response (ITT)

Parameter | Decitabine N=89 | Supportive Care N=81
Overall Response Rate (CR+PR)† Complete Response (CR) Partial Response (PR) | 15 (17%)** 8 (9%) 7 (8%) | 0 (0%) 0 (0%) 0 (0%)
Duration of Response Median time to (CR+PR) response - Days (range) Median Duration of (CR+PR) response - Days (range) | 93 (55 to 272) 288 (116 to 388) | NA NA

**p-value <0.001 from two-sided Fisher’s Exact Test comparing Decitabine vs. Supportive Care.
†In the statistical analysis plan, a p-value of ≤ 0.024 was required to achieve statistical significance.
All patients with a CR or PR were RBC and platelet transfusion independent in the absence of growth factors.

Responses occurred in patients with an adjudicated baseline diagnosis of AML.

14.2 Single-arm Studies in Myelodysplastic Syndrome

Three open-label, single-arm, multicenter studies were conducted to evaluate the safety and efficacy of decitabine in patients with MDS with any of the FAB subtypes. In one study conducted in North America, 99 patients with IPSS Intermediate-1, Intermediate-2, or high-risk prognostic scores received decitabine 20 mg/m^2 as an intravenous infusion over 1-hour daily, on days 1 to 5 of week 1 every 4 weeks (1 cycle). The results were consistent with the results of the controlled trial and are summarized in Table 8.

Table 7 Baseline Demographics and Other Patient Characteristics (ITT)

Demographic or Other Patient Characteristic | Decitabine N = 99
Age (years)
Mean (±SD) | 71±9
Median (Range: min-max) | 72 (34 to 87)
Sex n (%)
Male | 71 (72)
Female | 28 (28)
Race n (%)
White | 86 (87)
Black | 6 (6)
Asian | 4 (4)
Other | 3 (3)
Days From MDS Diagnosis to First Dose | 444±626
Mean (±SD) Median (Range: min-max) | 154 (7 to 3079)
Previous MDS Therapy n (%)
Yes | 27 (27)
No | 72 (73)
RBC Transfusion Status n (%)
Independent | 33 (33)
Dependent | 66 (67)
Platelet Transfusion Status n (%)
Independent | 84 (85)
Dependent | 15 (15)
IPSS Classification n (%)
Low Risk | 1 (1)
Intermediate–1 | 52 (53)
Intermediate–2 | 23 (23)
High Risk | 23 (23)
FAB Classification n (%)
RA | 20 (20)
RARS | 17 (17)
RAEB | 45 (45)
RAEB-t | 6 (6)
CMML | 11 (11)

Table 8 Analysis of Response (ITT)*

Parameter | Decitabine N=99
Overall Response Rate (CR+PR) Complete Response (CR) Partial Response (PR) | 16 (16%) 15 (15%) 1 (1%)
Duration of Response Median time to (CR+PR) response - Days (range) Median Duration of (CR+PR) response - Days (range) | 162 (50 to 267) 443 (72 to 722^+)

* Cheson BD, Bennett JM, et al. Report of an International Working Group to Standardize Response Criteria for MDS. Blood. 2000; 96:3671-3674.
^+indicates censored observation

15 REFERENCES

1. OSHA Hazardous Drugs.” OSHA.

http://www.osha.gov/SLTC/hazardousdrugs/index.html

16 HOW SUPPLIED/STORAGE AND HANDLING

DRUG PRODUCT

White to off white lyophilized powder in 20 mL colorless tubular glass single-dose vial with grey bromo butyl rubber stopper and sealed with baby blue flip top aluminum seal.

Each vial contains 50 mg decitabine. (NDC 47335-361-40)

DILUENT

Clear colorless solution filled in 10 mL colorless tubular glass vial with grey bromo butyl stopper sealed with transparent flip top aluminum seal.

Each vial contains 68 mg monobasic potassium phosphate, 11.6 mg sodium hydroxide and 10 mL water for injection. (NDC 47335-362-40)

The carton contains 1 vial of drug product, and 1 vial of sterile diluent. (NDC 47335-361-41)

Storage and Handling

Store at 20° to 25°C (68° to 77°F); excursions permitted between 15° and 30°C (59° and 86°F) [see USP Controlled Room Temperature].

17 PATIENT COUNSELING INFORMATION

Myelosuppression

Advise patients of the risk of myelosuppression and to report any symptoms of infection, anemia, or bleeding to their healthcare provider as soon as possible. Advise patients for the need for laboratory monitoring [see Warnings and Precautions (5.1)].

Embryo-Fetal Toxicity

Advise pregnant women of the potential risk to a fetus. Advise females of reproductive potential to inform their healthcare provider of a known or suspected pregnancy [see Warnings and Precautions (5.2) and Use in Specific Populations (8.1)].

Advise females of reproductive potential to use effective contraception while receiving Decitabine for Injection and for 6 months after last dose [see Use in Specific Populations (8.3)].

Advise males with female partners of reproductive potential to use effective contraception while receiving treatment with Decitabine for Injection and for 3 months after the last dose [see Use in Specific Populations (8.3) and Nonclinical Toxicology (13.1)].

Lactation

Advise women to avoid breastfeeding while receiving Decitabine for Injection and for at least 2 weeks after the last dose [see Use in Specific Populations (8.2)].

Distributed by:

Sun Pharmaceutical Industries, Inc.

Cranbury, NJ 08512

Manufactured by:

Sun Pharmaceutical Ind. Ltd.

Halol-Baroda Highway,

Halol-389 350, Gujarat, India.

ISS. 05/2020

PACKAGE LABEL.PRINCIPAL DISPLAY PANEL-Carton Label

NDC 47335-361-41
Decitabine for Injection
50 mg per vial
Further dilution is required. See package insert.
For intravenous infusion only
Sterile
Cytotoxic Agent
Stability: Unless used within 15 minutes of reconstitution, the diluted solution must be
prepared using cold (2˚C to 8˚C) infusion fluids and stored at 2˚C to 8˚C (36˚F to 46˚F)
for up to a maximum of 7 hours until administration.
This carton contains:

- 1 vial of Decitabine for Injection
- 1 vial of Diluent

Rx Only
Single-dose vial
SUN PHARMA